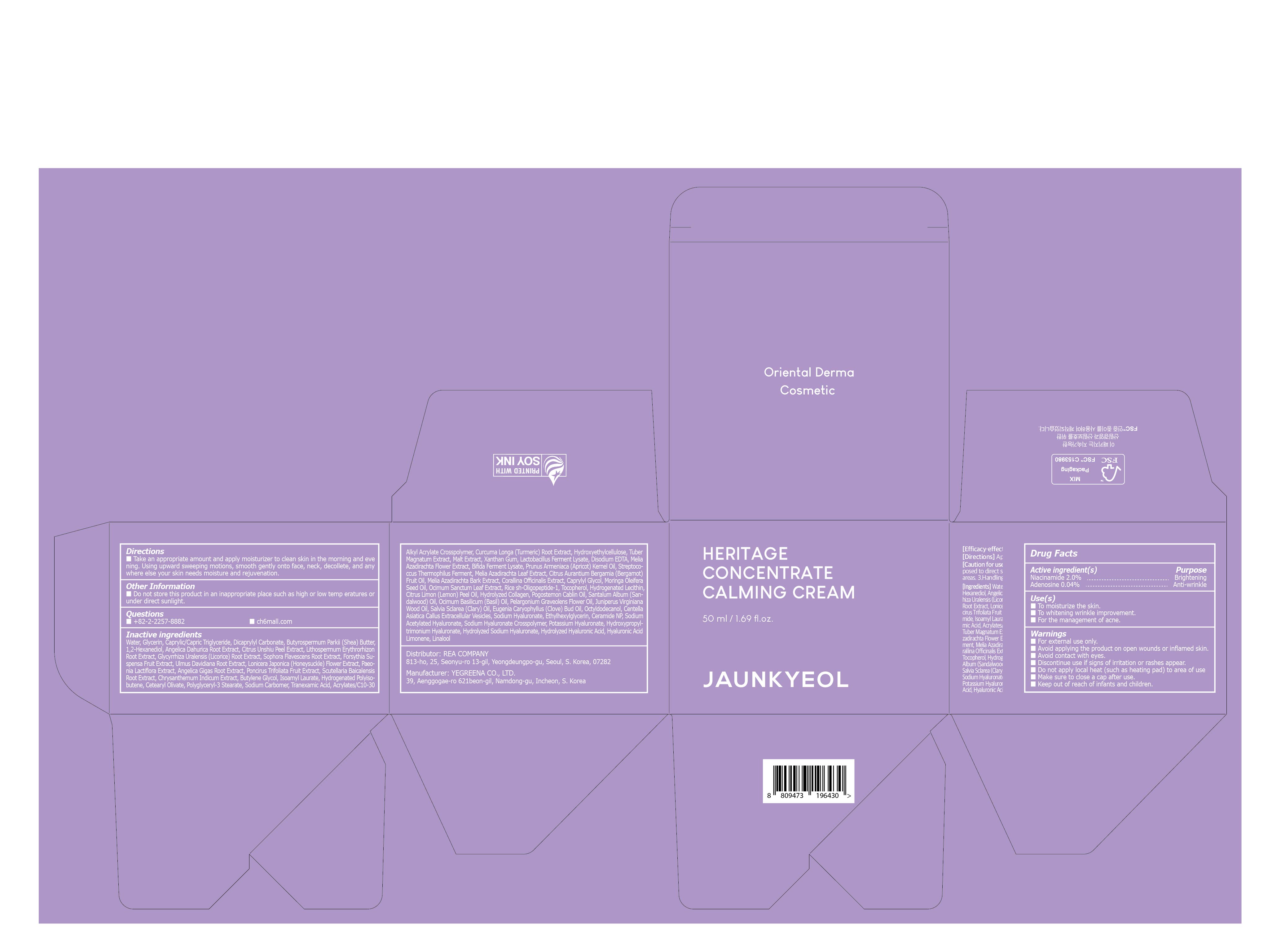 DRUG LABEL: JAUNKYEOL HERITAGE CONCENTRATE CALMING
NDC: 82916-170 | Form: CREAM
Manufacturer: Rea Company
Category: otc | Type: HUMAN OTC DRUG LABEL
Date: 20230222

ACTIVE INGREDIENTS: Niacinamide 2.0 g/100 mL; Adenosine 0.04 g/100 mL
INACTIVE INGREDIENTS: Water; Glycerin

ACTIVE INGREDIENTS

Niacinamide 2%
Adenosine 0.04%

PURPOSE

Skin Brightening
Anti-Wrinkle

Use(s)

■ To moisturize the skin
■ To whitening wrinkle improvement
■ For the management of acne.

Warnings

■ For external use only
■ Avoid applying the product on open wounds or inflamed skin.
■ Avoid contact with eyes.
■ Discontinue use if signs of irritation or rashes appear.
■ Do not apply local heat (such as heating pad) to area of use
■ Make sure to close a cap after use.
■ Keep out of reach of infants and children.

KEEP OUT OF REACH OF CHILDREN

■ Keep out of reach of infants and children.

Directions

■ Take an appropriate amount and apply moisturizer to clean skin in the morning and evening. Using upward sweeping motions, smooth gently onto face, neck, decollete, and anywhere else your skin needs moisture and rejuvenation.

Other Information

■ Do not store this product in an inappropriate place such as high or low temperatures or under direct sun light

Questions

■ +82-2-2257-8882
■ https://jaunmall.com/

Inactive ingredients

Water, Glycerin, Caprylic/Capric Triglyceride, Dicaprylyl Carbonate, Butyrospermum Parkii (Shea) Butter, 1,2-Hexanediol, Angelica Dahurica Root Extract, Citrus Unshiu Peel Extract, Lithospermum Erythrorhizon Root Extract, Glycyrrhiza Uralensis (Licorice) Root Extract, Sophora Flavescens Root Extract, Forsythia Suspensa Fruit Extract, Ulmus Davidiana Root Extract, Lonicera Japonica (Honeysuckle) Flower Extract, Paeonia Lactiflora Extract, Angelica Gigas Root Extract, Poncirus Trifoliata Fruit Extract, Scutellaria Baicalensis Root Extract, Chrysanthemum Indicum Extract, Butylene Glycol, Isoamyl Laurate, Hydrogenated Polyisobutene, Cetearyl Olivate, Polyglyceryl-3 Stearate, Sodium Carbomer, Tranexamic Acid, Acrylates/C10-30 Alkyl Acrylate Crosspolymer, Curcuma Longa (Turmeric) Root Extract, Hydroxyethylcellulose, Tuber Magnatum Extract, Malt Extract, Xanthan Gum, Lactobacillus Ferment Lysate, Disodium EDTA, Melia Azadirachta Flower Extract, Bifida Ferment Lysate, Prunus Armeniaca (Apricot) Kernel Oil, Streptococcus Thermophilus Ferment, Melia Azadirachta Leaf Extract, Citrus Aurantium Bergamia (Bergamot) Fruit Oil, Melia Azadirachta Bark Extract, Corallina Officinalis Extract, Caprylyl Glycol, Moringa Oleifera Seed Oil, Ocimum Sanctum Leaf Extract, Rice sh-Oligopeptide-1, Tocopherol, Hydrogenated Lecithin, Citrus Limon (Lemon) Peel Oil, Hydrolyzed Collagen, Pogostemon Cablin Oil, Santalum Album (Sandalwood) Oil, Ocimum Basilicum (Basil) Oil, Pelargonium Graveolens Flower Oil, Juniperus Virginiana Wood Oil, Salvia Sclarea (Clary) Oil, Eugenia Caryophyllus (Clove) Bud Oil, Octyldodecanol, Centella Asiatica Callus Extracellular Vesicles, Sodium Hyaluronate, Ethylhexylglycerin, Ceramide NP, Sodium Acetylated Hyaluronate, Sodium Hyaluronate Crosspolymer, Potassium Hyaluronate, Hydroxypropyltrimonium Hyaluronate, Hydrolyzed Sodium Hyaluronate, Hydrolyzed Hyaluronic Acid, Hyaluronic Acid, Limonene, Linalool